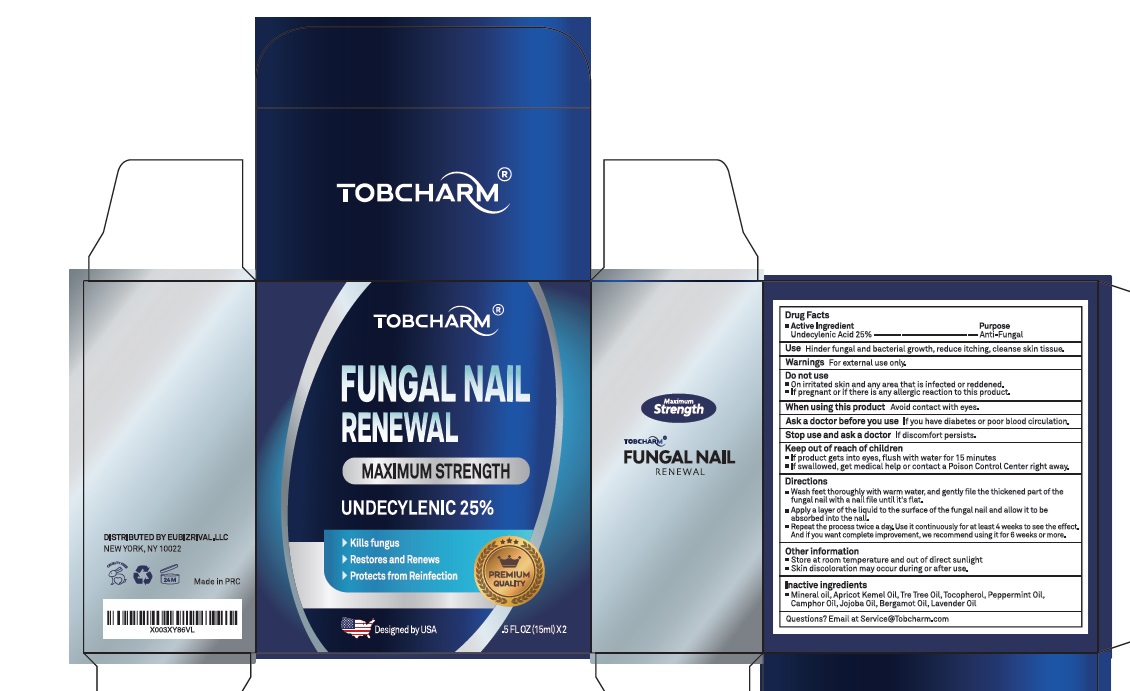 DRUG LABEL: Tobcharm
NDC: 83462-016 | Form: LIQUID
Manufacturer: Eubizrival LLC
Category: otc | Type: HUMAN OTC DRUG LABEL
Date: 20231220

ACTIVE INGREDIENTS: UNDECYLENIC ACID 24.8 g/100 mL
INACTIVE INGREDIENTS: MINERAL OIL; APRICOT KERNEL OIL; TEA TREE OIL; TOCOPHEROL; PEPPERMINT OIL; CAMPHOR OIL; JOJOBA OIL; BERGAMOT OIL; LAVENDER OIL

Active Ingredient

UNDECYLENIC ACID 24.8%

Purpose

Anti-Fungal

Use

Hinder fungal and bacterial growth, reduce itching, cleanse skin tissue.

Warnings

For external use only.

Do not use

- On irritated skin and any area that is infected or reddened.
- If pregnant or if there is any allergic reaction to this product.

When using this product Avoid contact with eyes.

Ask a doctor before you useIf you have diabetes or poor blood circulation.

Stop use and ask a doctorif discomfort persists.

Keep out of reach of children

- If product gets into eyes, flush with water for 15 minutes
- If swallowed, get medical help or contact a Poison Control Center right away.

Directions

- Wash feet throughly with warm water, and get gently file the thickened part of the fungal nail with a nail file until its flat.
- Apply a layer of the liquid to the surface of the fungal nail and allow it to be absorbed into the nail.
- Repeate the process twice a day . Use it continuously for atleast 4 weeks to see the effect And if you want complete improvement , we recommend using it for 6 weeks or more.

Other information

- Store at room temperature and out of direct sunlight
- Skin discoloration may occur during or after use

Inactive ingredients

mineral oil, apricot kernel oil, tea tree oil, tocopherol, peppermint oil, camphor oil, jojoba oil, bergamot oil, lavender oil